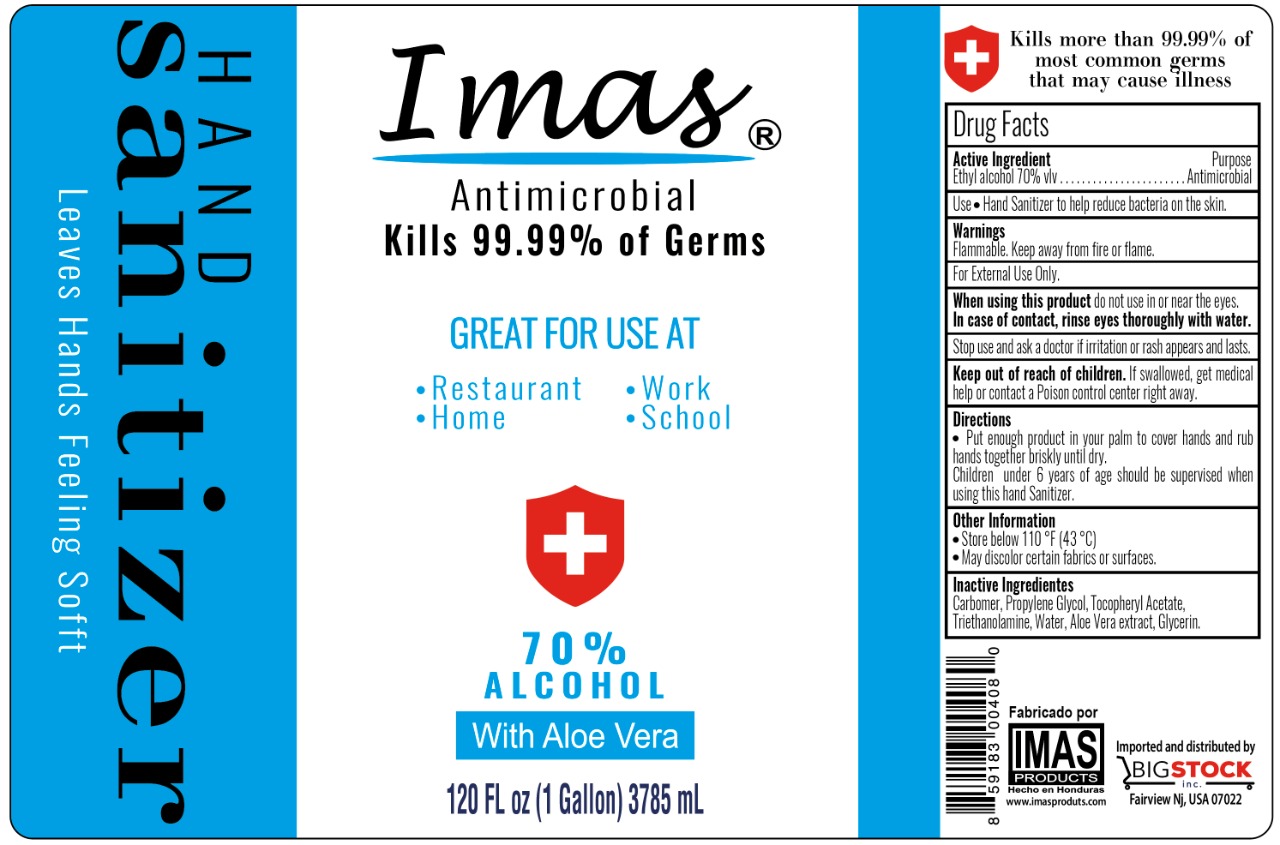 DRUG LABEL: Imas
NDC: 78866-815 | Form: GEL
Manufacturer: Stock, S.A. de C.V.
Category: otc | Type: HUMAN OTC DRUG LABEL
Date: 20200606

ACTIVE INGREDIENTS: ALCOHOL 70 mL/100 mL
INACTIVE INGREDIENTS: ALPHA-TOCOPHEROL ACETATE; TROLAMINE; ALOE VERA LEAF; CARBOMER 940; GLYCERIN 1.45 mL/100 mL; PROPYLENE GLYCOL; WATER

Stock, S.A. de C.V. IMAS-GEL

Active Ingredient(s)

Alcohol 70% v/v. Purpose: Antiseptic

Purpose

Antiseptic, Hand Sanitizer

Use

Hand Sanitizer to help reduce bacteria that potentially can cause disease.

Warnings

For external use only. Flammable. Keep away from heat or flame

When using this product keep out of eyes, ears, and mouth. In case of contact with eyes, rinse eyes thoroughly with water.
Stop use and ask a doctor if irritation or rash occurs. These may be signs of a serious condition.
Keep out of reach of children. If swallowed, get medical help or contact a Poison Control Center right away.

Stop use and ask a doctor if irritation or rash occurs. These may be signs of a serious condition.

Keep out of reach of children. If swallowed, get medical help or contact a Poison Control Center right away.

Directions

- Place enough product on hands to cover hands and rub hands together briskly until dry.
- Children under 6 years of age should be supervised when using this hand sanitizer.

Other information

Store below 110F(43C)

May discolor certain fabrics or surfaces.

Inactive ingredients

Carbomer, propylene glycol, tocopheryl acetate, triethanolamine, water, Aloe vera extract, glycerin

Package Label - Principal Display Panel

3785 mL NDC: 78866-815-05